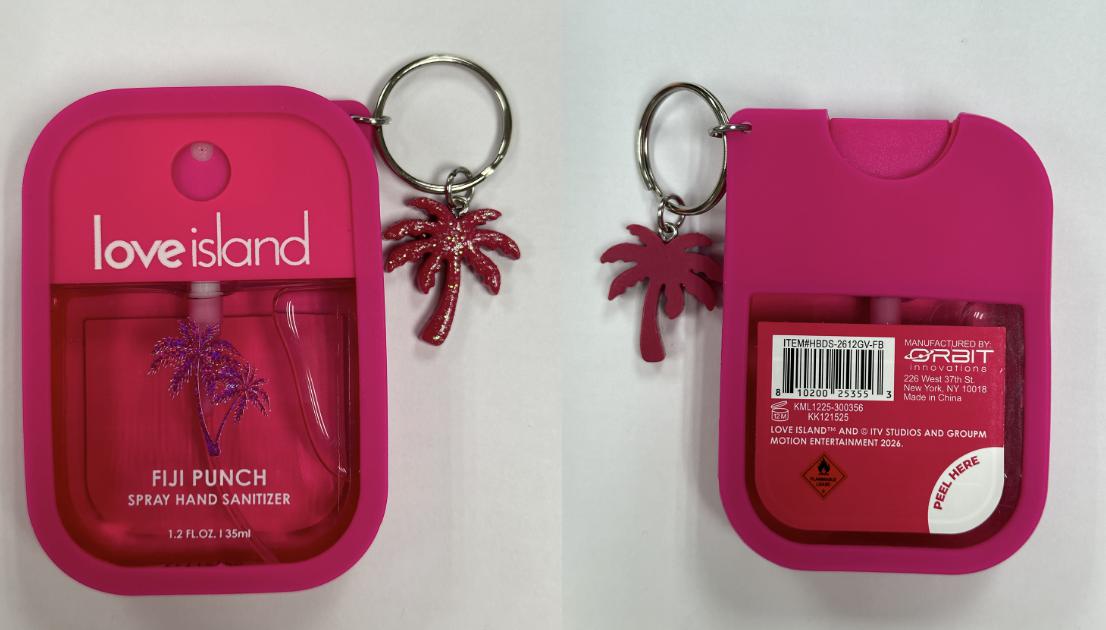 DRUG LABEL: Fiji Punch Hand Sanitizer
NDC: 73928-128 | Form: LIQUID
Manufacturer: Kingkey MBC Life Technology Group Co.,Ltd
Category: otc | Type: HUMAN OTC DRUG LABEL
Date: 20260102

ACTIVE INGREDIENTS: ALCOHOL 62 mL/100 mL
INACTIVE INGREDIENTS: CI 16035; CI 17200; GLYCERIN; WATER; FRAGRANCE 13576

FIJI PUNCN SPRAY HAND SANITIZER

Active ingredient

Alcohol 62% ------------------------------- Antibacterial

Users

Hand Sanitizer to help reduce bacteria that potentially can cause disease.

For use when soap and water are not available.

Purpose

Uses

Hand Sanitizer to help reduce bacteria that potentially can cause disease. For use when soap and water are not available

Warnings

Flammable. Keep away from fire or flame.

For external use only.

Do not use it

near eye area. In case of contact, rinse eyes thoroughly with water.

Stop use and ask a doctor if irritation or rash appears and lasts.

Keep out of reach of children.

Keep out of reach of children.

If swallowed, get medical help or contact a Poison Control Center right away.

Directions

■ Apply into hand and thoroughly spreadon both hands, rub until dry.

■ Supervise children under 6 years of age when using this product to avoid swallowing

Inactives ingredient

Water
GLYCERIN
ALCOHOL
Fragrance
CI 17200
CI 16035

Other information

■ Store between 15 - 30°C (59 - 86°F)

■ Avoid freezing and excessive heat above 40°C (104°F)

Questions or comments？

call toll free 212-68906008